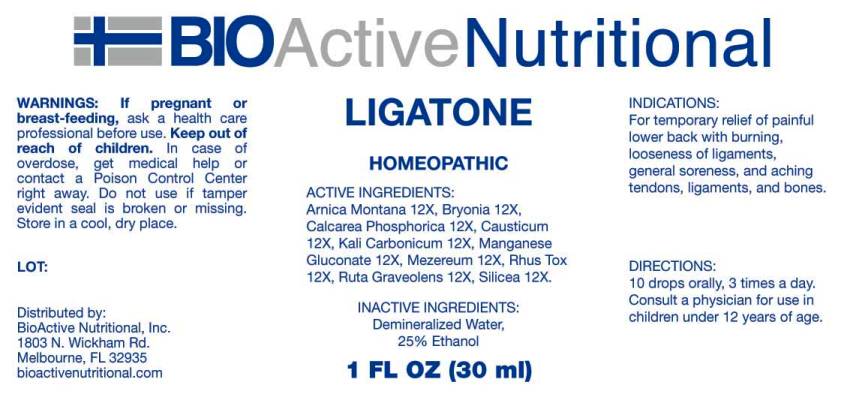 DRUG LABEL: Ligatone
NDC: 43857-0001 | Form: LIQUID
Manufacturer: BioActive Nutritional, Inc.
Category: homeopathic | Type: HUMAN OTC DRUG LABEL
Date: 20160414

ACTIVE INGREDIENTS: ARNICA MONTANA 12 [hp_X]/1 mL; BRYONIA ALBA ROOT 12 [hp_X]/1 mL; TRIBASIC CALCIUM PHOSPHATE 12 [hp_X]/1 mL; CAUSTICUM 12 [hp_X]/1 mL; POTASSIUM CARBONATE 12 [hp_X]/1 mL; MANGANESE GLUCONATE 12 [hp_X]/1 mL; DAPHNE MEZEREUM BARK 12 [hp_X]/1 mL; TOXICODENDRON PUBESCENS LEAF 12 [hp_X]/1 mL; RUTA GRAVEOLENS FLOWERING TOP 12 [hp_X]/1 mL; SILICON DIOXIDE 12 [hp_X]/1 mL
INACTIVE INGREDIENTS: WATER; ALCOHOL

Drug Facts:

ACTIVE INGREDIENTS:

Arnica montana 12X, Bryonia 12X, Calcarea phosphorica 12X, Causticum 12X, Kali carbonicum 12X, Manganese gluconate 12X, Mezereum 12X, Rhus tox 12X, Ruta graveolens 12X, Silicea 12X.

INDICATIONS:

For temporary relief of painful lower back with burning, looseness of ligaments, general soreness, and aching tendons, ligaments, and bones.

WARNINGS:

If pregnant or breast-feeding, ask a health care professional before use.

Keep out of reach of children. In case of overdose, get medical help or contact a Poison Control Center right away.

Do not use if tamper evident seal is broken or missing.

Store in a cool, dry place.

DIRECTIONS:

10 drops orally, 3 times a day. Consult a physician for use in children under 12 years of age.

INACTIVE INGREDIENTS:

Demineralized water, 25% Ethanol.

Keep out of reach of children. In case of overdose, get medical help or contact a Poison Control Center right away.

INDICATIONS:

For temporary relief of painful lower back with burning, looseness of ligaments, general soreness, and aching tendons, ligaments, and bones.

QUESTIONS:

Distributed by:
BioActive Nutritional, Inc.
1803 N. Wickham Rd.
Melbourne, FL 32935
bioactivenutritional.com

PACKAGE LABEL DISPLAY:

BIOActive Nutritional

LIGATONE

HOMEOPATHIC

1 FL OZ (30 ml)